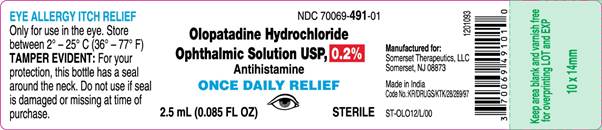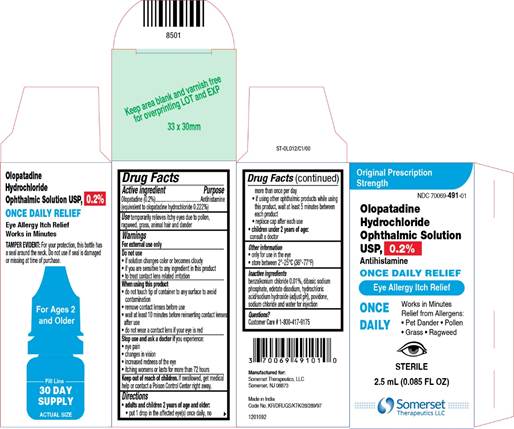 DRUG LABEL: OLOPATADINE HYDROCHLORIDE
NDC: 70069-491 | Form: SOLUTION/ DROPS
Manufacturer: Somerset Therapeutics, LLC
Category: otc | Type: HUMAN OTC DRUG LABEL
Date: 20241221

ACTIVE INGREDIENTS: OLOPATADINE HYDROCHLORIDE 2 mg/1 mL
INACTIVE INGREDIENTS: BENZALKONIUM CHLORIDE; POVIDONE, UNSPECIFIED; SODIUM PHOSPHATE, DIBASIC, UNSPECIFIED FORM; SODIUM CHLORIDE; EDETATE DISODIUM; SODIUM HYDROXIDE; HYDROCHLORIC ACID; WATER

Olopatadine Hydrochloride Ophthalmic Solution, USP, 0.2%
ONCE DAILY RELIEF

Drug Facts

Active Ingredients | Purpose
Olopatadine 0.2% (equivalent to olopatadine hydrochloride 0.222%) | Antihistamine

INDICATIONS AND USAGE

Use temporarily relieves itchy eyes due to pollen, ragweed, grass, animal hair and dander

Warnings

For external use only

Do not use

- if solution changes color or becomes cloudy
- if you are sensitive to any ingredient in this product
- to treat contact lens related irritation

When using this product

- do not touch tip of container to any surface to avoid contamination
- remove contact lenses before use
- wait at least 10 minutes before reinserting contact lenses after use
- do not wear a contact lens if your eye is red

Stop use and ask a doctor if you experience:

- eye pain
- changes in vision
- increased redness of the eye
- itching worsens or lasts for more than 72 hours

Keep out of reach of children. If swallowed, get medical help or contact a Poison Control Center right away.

Directions

- adults and children 2 years of age and older:
- put 1 drop in the affected eye(s) once daily, no more than once per day
- if using other ophthalmic products while using this product, wait at least 5 minutes between each product
- replace cap after each use
- children under 2 years of age:consult a doctor

Other information

- only for use in the eye
- store between 2°-25°C (36°-77°F)

Inactive ingredients

benzalkonium chloride 0.01%, dibasic sodium phosphate, edetate disodium, hydrochloric acid/sodium hydroxide (adjust pH), povidone, sodium chloride and water for injection

Questions?

Customer Care # 1-800-417-9175

Manufactured for:

Somerset Therapeutics, LLC

Somerset, NJ 08873

Made in India

Code No.:KR/DRUGS/KTK/28/289/97

1201094

ST-OLO12/P/00

Container Label

NDC 70069-491-01

Olopatadine Hydrochloride Ophthalmic Solution USP, 0.2%

Antihistamine

ONCE DAILY RELIEF

Sterile

2.5 mL (0.085 FL OZ)

Carton Label

Original Prescription Strength

NDC 70069-491-01

Olopatadine Hydrochloride Ophthalmic Solution USP, 0.2%

Antihistamine

ONCE DAILY RELIEF

Eye Allergy Itch Relief

ONCE DAILY

Works in Minutes

Relief from Allergens:

• Pet Dander

• Pollen

• Grass

• Ragweed

Sterile

2.5 mL (0.085 FL OZ)